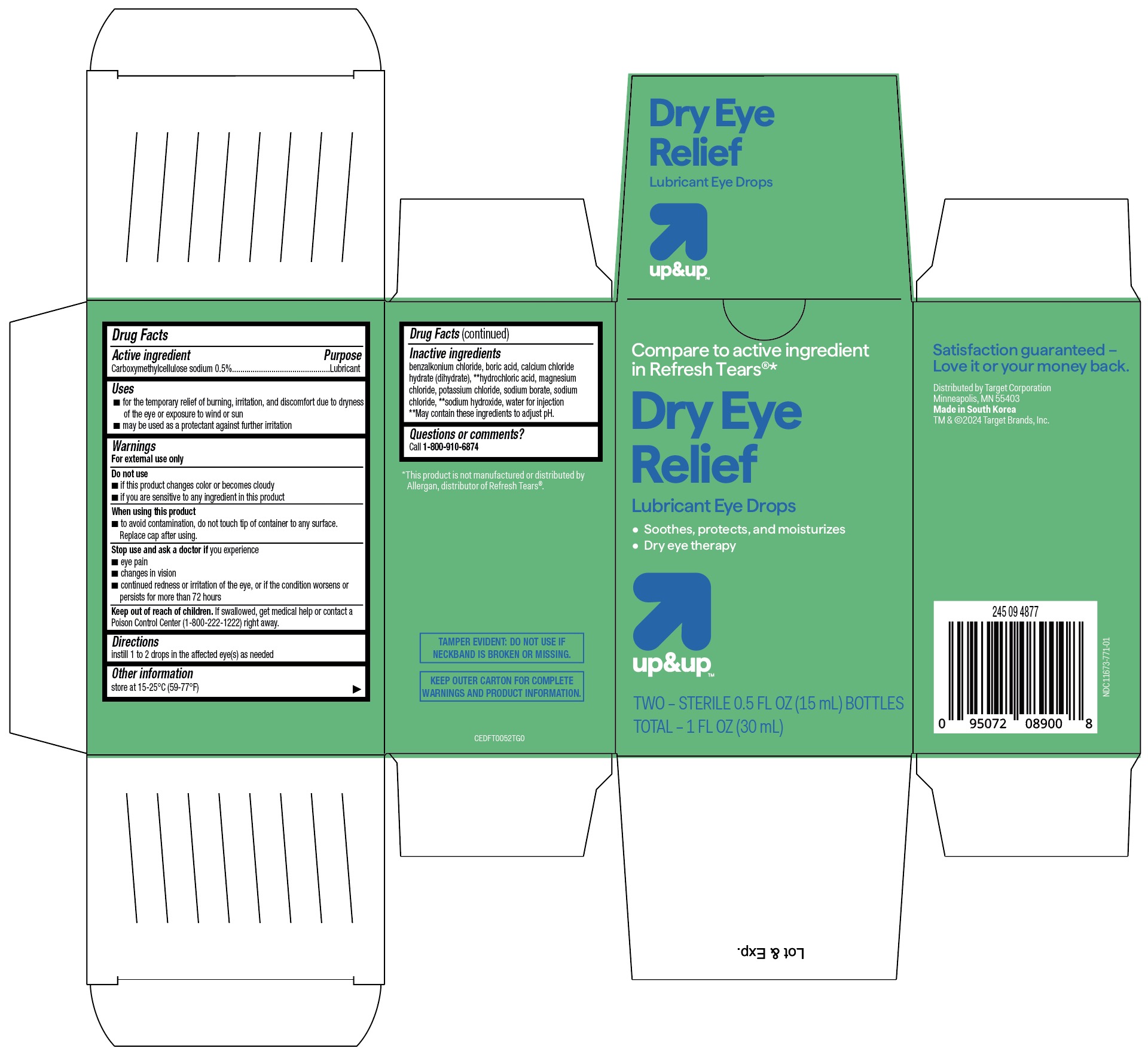 DRUG LABEL: Up and Up Dry Eye Relief Lubricant Eye Drops
NDC: 11716-0771 | Form: SOLUTION/ DROPS
Manufacturer: Hanlim
Category: otc | Type: HUMAN OTC DRUG LABEL
Date: 20251025

ACTIVE INGREDIENTS: CARBOXYMETHYLCELLULOSE SODIUM 5 mg/1 mL
INACTIVE INGREDIENTS: SODIUM BORATE; WATER; SODIUM CHLORIDE; CALCIUM CHLORIDE; HYDROCHLORIC ACID; MAGNESIUM CHLORIDE; SODIUM HYDROXIDE; BENZALKONIUM CHLORIDE; BORIC ACID; POTASSIUM CHLORIDE

Up & Up Dry Eye Relief Lubricant Eye Drops- Twin Pack (MFG Listing for PLD)

ACTIVE INGREDIENT

Carboxymethylcellulose Sodium 0.5%

Purpose.......Lubricant

KEEP OUT OF REACH OF CHILDREN

If swallowed, get medical help or contact a Poison Control Center immediately (1-800-222-1222) right away.

DOSAGE AND ADMINISTRATION

Instill 1 or 2 drops in the affected eye(s) as needed

INDICATIONS AND USAGE

- For the temporary relief of burning, irritation, and discomfort due to dryness of the eye or from irritation from wind or sun.
- May be used to protect against further irritation.

WARNINGS

- Warnings - For external use only.

DO NOT USE

- Do not use - if solution changes color or becomes cloudy
- If you are sensitive or allergic to any ingredient in this product

WHEN USING

- To avoid contamination, do not touch tip of container to any surface.
- Replace cap after using.

STOP USE
Stop use and ask a doctor if

- you experience eye pain
- changes in vision occur
- redness or irritation of the eye(s) gets worse or lasts more than 72 hours

INACTIVE INGREDIENT

Inactive ingredients: benzalkonium chloride, boric acid, calcium chloride hydrate, hydrochloric acid, magnesium chloride, potassium chloride, sodium borate, sodium chloride, sodium hydroxide, water